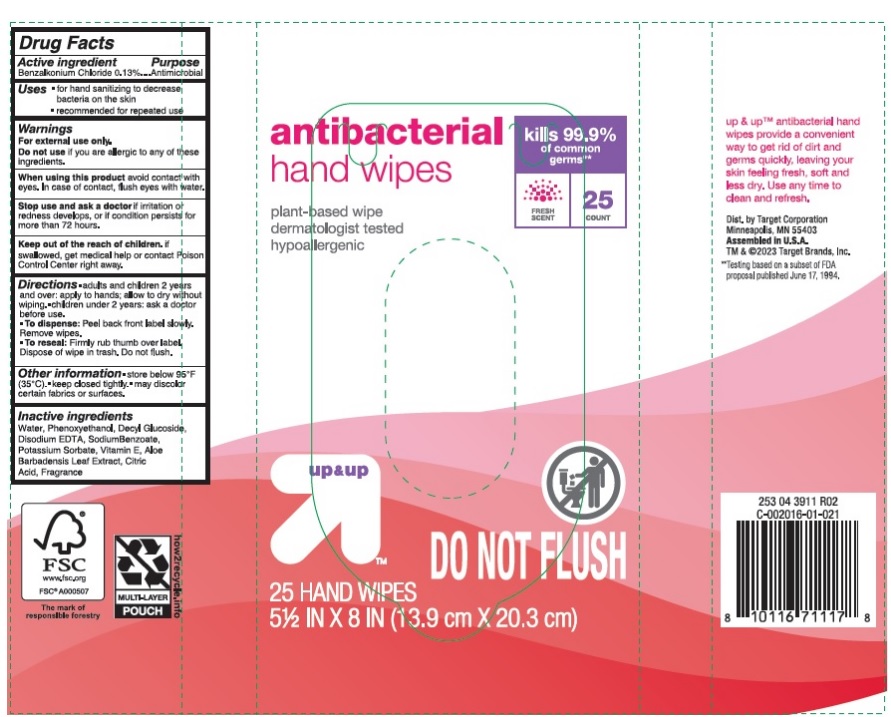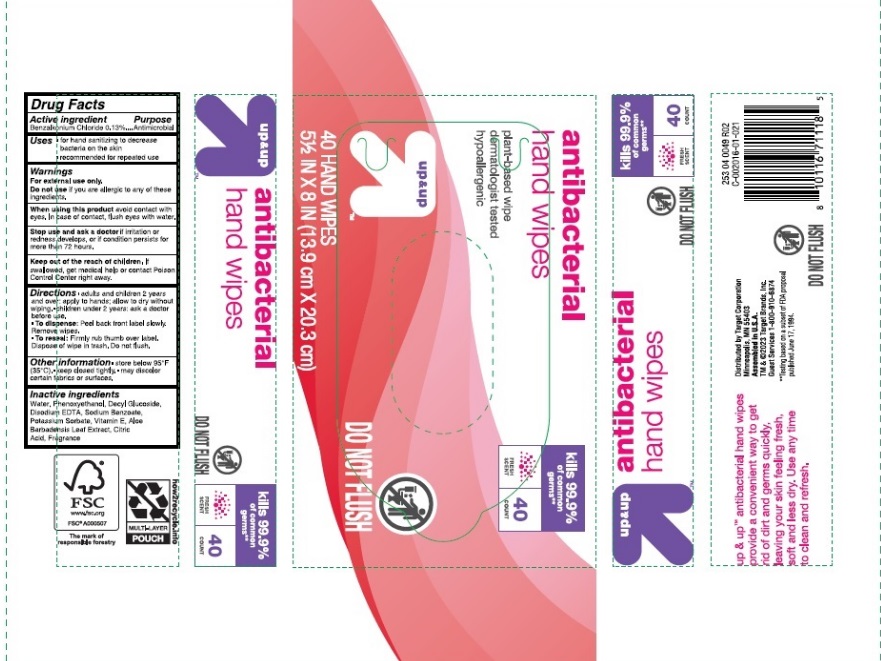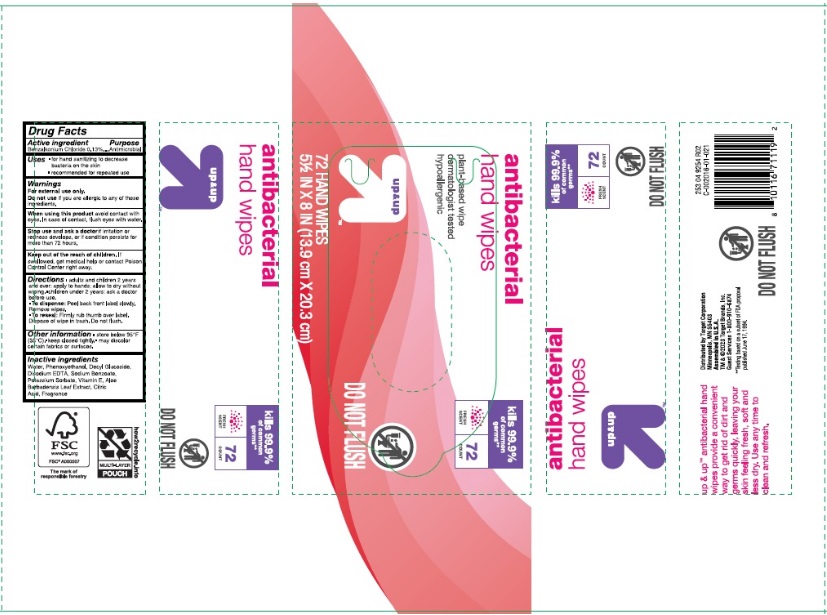 DRUG LABEL: Benzalkonium Chloride
NDC: 82442-250 | Form: CLOTH
Manufacturer: Target Corporation
Category: otc | Type: HUMAN OTC DRUG LABEL
Date: 20251205

ACTIVE INGREDIENTS: BENZALKONIUM CHLORIDE 0.13 g/100 1
INACTIVE INGREDIENTS: ALOE VERA LEAF; CITRIC ACID MONOHYDRATE; EDETATE DISODIUM ANHYDROUS; POTASSIUM SORBATE; PHENOXYETHANOL; WATER; SODIUM BENZOATE; DECYL GLUCOSIDE

Antibacterial Hand Wipes

Active ingredient

Benzalkonium Chloride 0.13%

Purpose

Antimicrobial

Uses

- for hand sanitizing to decrease bacteria on the skin
- recommended for repeated use

Warnings

For external use only.

Do not use

if you are allergic to any of these ingredients.

When using this product

avoid contact with eyes. In case of contact, flush eyes with water.

Stop use and ask a doctor

if irritation or redness develops, or if condition persists for more than 72 hours.

Keep out of reach of children.

If swallowed, get medical help or contact Poison Control Center right away.

Directions

- adults and children 2 years and over: apply to hands; allow to dry without wiping.
- Children under 2 years: ask a doctor before use.
- To dispense: Peel back front label slowly. Remove wipes.
- To reseal: Firmly rub thumb over label. Dispose of wipe in trash. Do not flush.

Other information

- store below 95°F (35°C)
- keep closed tightly
- may discolor certain fabrics or surfaces.

Inactive ingredients

Water, Phenoxyethanol, Decyl Glucoside, Disodium EDTA, Sodium Benzoate, Potassium Sorbate, Vitamin E, Aloe Barbadensis Leaf Extract, Citric Acid, Fragrance

PACKAGE LABEL

antibacterial

hand wipes

plant-based wipes

dermatologist tested

hypoallergenic

25 HAND WIPES

5½ IN X 8 IN

40 HAND WIPES

5½ IN X 8 IN

72 HAND WIPES

5½ IN X 8 IN